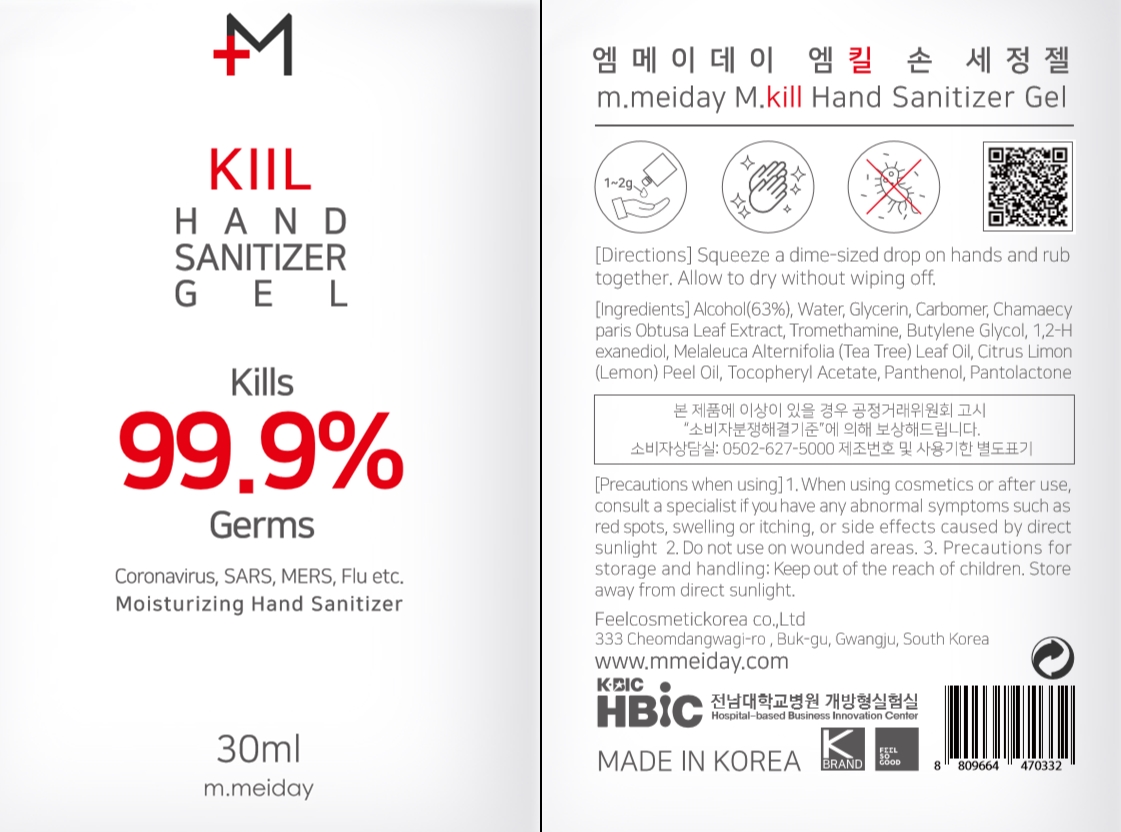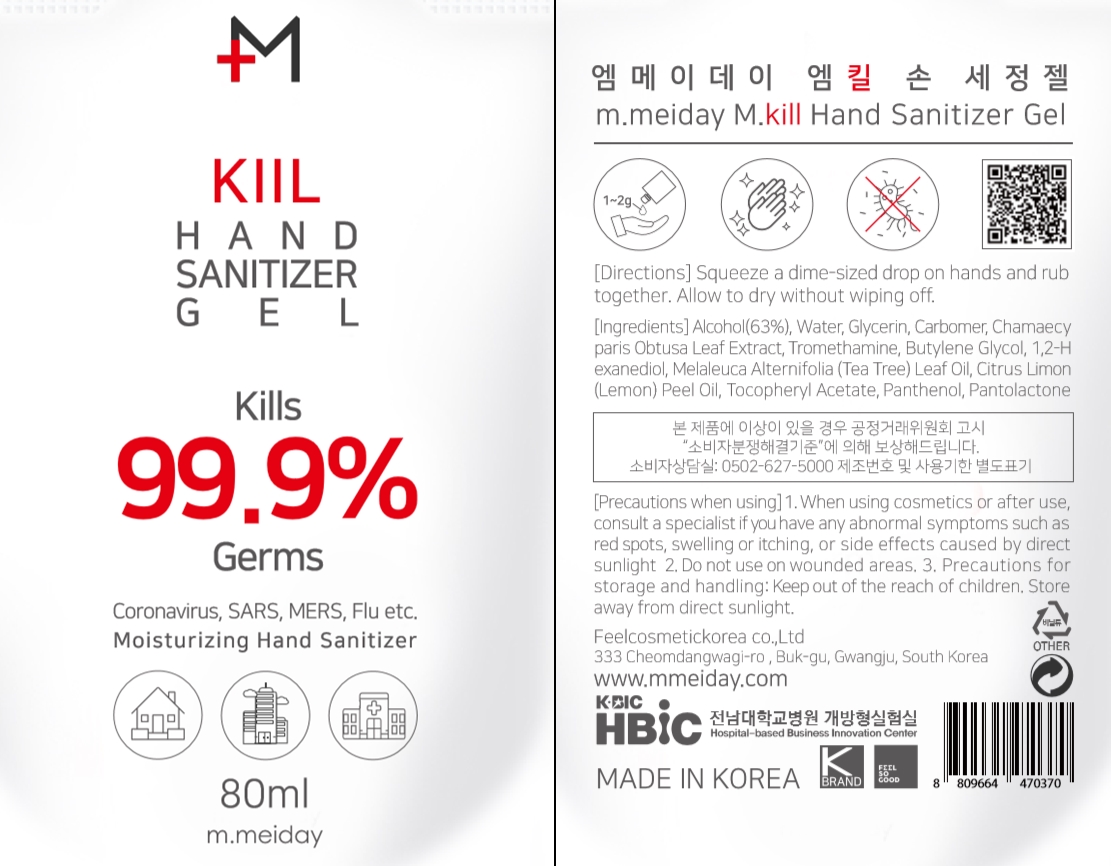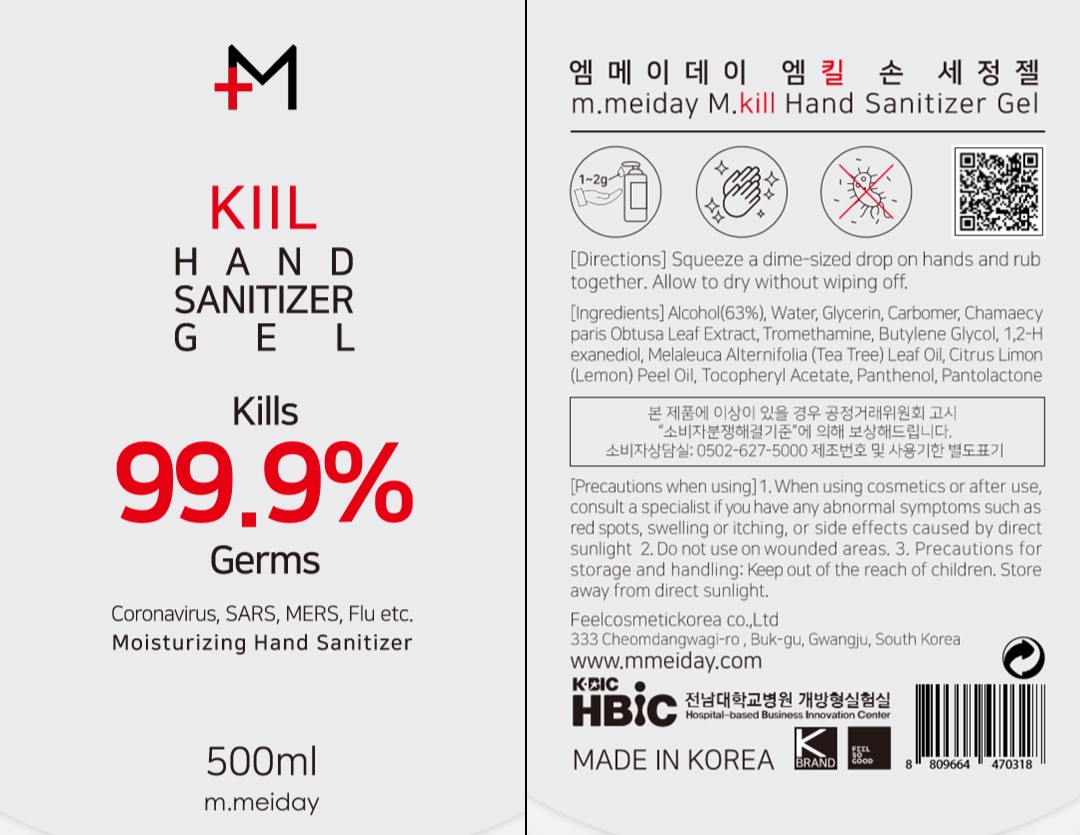 DRUG LABEL: m.meiday M.kill Hand Sanitizer Gel
NDC: 74454-317 | Form: GEL
Manufacturer: FEEL COSMETIC KOREA CO., LTD
Category: otc | Type: HUMAN OTC DRUG LABEL
Date: 20200413

ACTIVE INGREDIENTS: ALCOHOL 63 mL/100 mL
INACTIVE INGREDIENTS: BUTYLENE GLYCOL 0.2 mL/100 mL; PANTOLACTONE, (R)- 0.001 mL/100 mL; CARBOMER HOMOPOLYMER, UNSPECIFIED TYPE 0.5 mL/100 mL; 1,2-HEXANEDIOL 0.2 mL/100 mL; TROMETHAMINE 0.1 mL/100 mL; TEA TREE OIL 0.1 mL/100 mL; ALPHA-TOCOPHEROL ACETATE 0.1 mL/100 mL; WATER 32.349 mL/100 mL; GLYCERIN 3 mL/100 mL; CHAMAECYPARIS OBTUSA LEAF 0.3 mL/100 mL; LEMON OIL 0.1 mL/100 mL; PANTHENOL 0.05 mL/100 mL

Directions

Squeeze a dime-sized drop on hands and rub together. Allow to dry without wiping off.

Active Ingredient

Alcohol 62%

Purpose

Anticeptic

Ingredients

Water, Glycerin, Carbomer, Chamaecy paris Obtusa Leaf Extract, Tromethamine, Butylene Glycol, 1,2-H exanediol, Melaleuca Alternifolia (Tea Tree) Leaf Oil, Citrus Limon (Lemon) Peel Oil, Tocopheryl Acetate, Panthenol, Pantolactone

Precautions when using

1. When using cosmetics or after use, consult a specialist if you have any abnormal symptoms such as red spots, swelling or itching, or side effects caused by direct sunlight

Precautions when using

2. Do not use on wounded areas.

Precautions when using

Precautions for storage and handling. Store away from direct sunlight.

Precautions when using

Keep out of the reach of children.

Warnings

For external Use Only. Flammable. Keep away from fire or flame.

Use

Hand Sanitizer to help reduce bacteria that potentially can cause disease. For use when soap and water are not available.